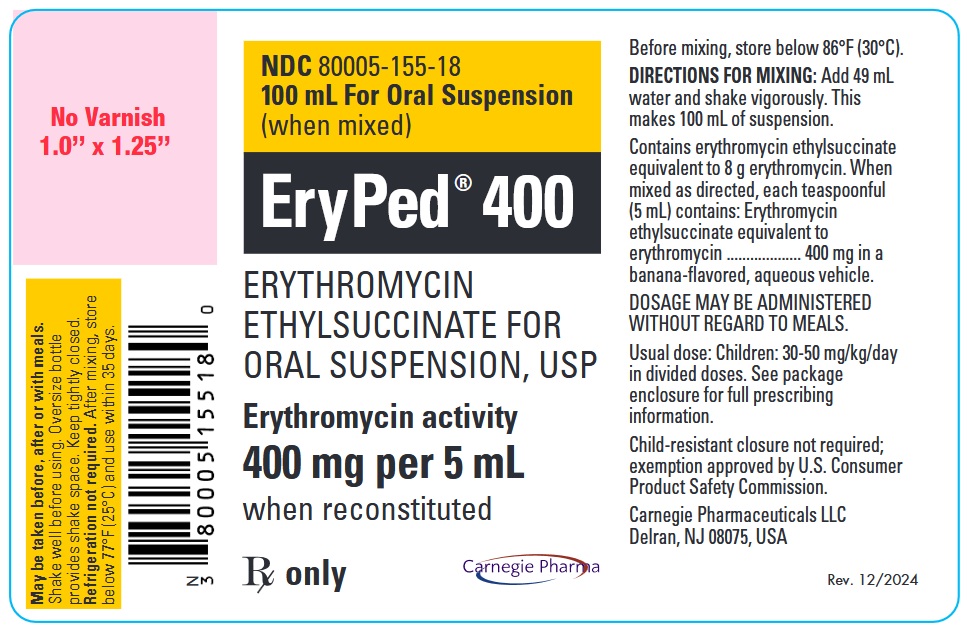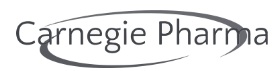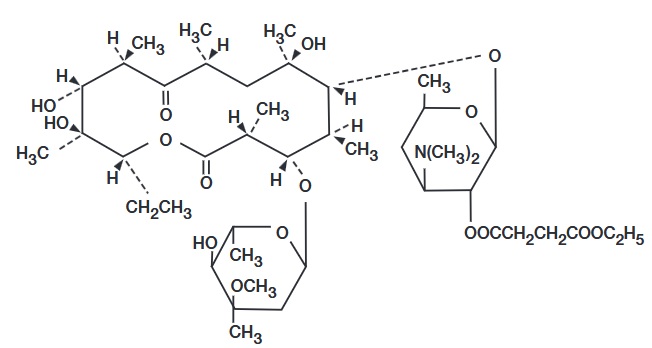 DRUG LABEL: Ery-Ped
NDC: 80005-155 | Form: SUSPENSION
Manufacturer: Carnegie Pharmaceuticals LLC
Category: prescription | Type: HUMAN PRESCRIPTION DRUG LABEL
Date: 20241224

ACTIVE INGREDIENTS: ERYTHROMYCIN ETHYLSUCCINATE 400 mg/5 mL
INACTIVE INGREDIENTS: CARAMEL; POLYSORBATE 80; SODIUM CITRATE; SUCROSE; XANTHAN GUM

ERY-PED®
(ERYTHROMYCIN
ETHYLSUCCINATE, USP)

Rx only

To reduce the development of drug-resistant bacteria and maintain the effectiveness of Ery-Ped and other antibacterial drugs, Ery-Ped should be used only to treat or prevent infections that are proven or strongly suspected to be caused by bacteria.

DESCRIPTION

Erythromycin is produced by a strain of Saccharopolyspora erythraea (formerly Streptomyces erythraeus) and belongs to the macrolide group of antibiotics. It is basic and readily forms salts with acids. The base, the stearate salt, and the esters are poorly soluble in water. Erythromycin ethylsuccinate is an ester of erythromycin suitable for oral administration. Erythromycin ethylsuccinate is known chemically as erythromycin 2'-(ethyl succinate). The molecular formula is C43H75NO16 and the molecular weight is 862.06. The structural formula is:

Ery-Ped 200 (erythromycin ethylsuccinate for oral suspension) when reconstituted with water, forms a suspension containing erythromycin ethylsuccinate equivalent to 200 mg erythromycin per 5 mL (teaspoonful) or 100 mg per 2.5 mL (dropperful) with an appealing fruit flavor. Ery-Ped 400 when reconstituted with water, forms a suspension containing erythromycin ethylsuccinate equivalent to 400 mg of erythromycin per 5 mL (teaspoonful) with an appealing banana flavor.

These products are intended primarily for pediatric use but can also be used in adults.

Inactive Ingredients

Ery-Ped 200, Ery-Ped 400:

Caramel, polysorbate, sodium citrate, sucrose, xanthan gum and artificial flavors.

CLINICAL PHARMACOLOGY

Orally administered erythromycin ethylsuccinate suspension is readily and reliably absorbed under both fasting and nonfasting conditions.

Erythromycin diffuses readily into most body fluids. Only low concentrations are normally achieved in the spinal fluid, but passage of the drug across the blood-brain barrier increases in meningitis. In the presence of normal hepatic function, erythromycin is concentrated in the liver and excreted in the bile; the effect of hepatic dysfunction on excretion of erythromycin by the liver into the bile is not known. Less than 5 percent of the orally administered dose of erythromycin is excreted in active form in the urine.

Erythromycin crosses the placental barrier, but fetal plasma levels are low. The drug is excreted in human milk.

Microbiology

Mechanism of Action

Erythromycin acts by inhibition of protein synthesis by binding 50 S ribosomal subunits of susceptible organisms. It does not affect nucleic acid synthesis. Antagonism has been demonstrated in vitro between erythromycin and clindamycin, lincomycin, and chloramphenicol.

Resistance

Many strains of Haemophilus influenzae are resistant to erythromycin alone but are susceptible to erythromycin and sulfonamides used concomitantly.

Interactions With Other Antimicrobials

Staphylococci resistant to erythromycin may emerge during a course of therapy.

Antimicrobial Activity

Erythromycin has been shown to be active against most strains of the following microorganisms, both in vitro and in clinical infections as described in the INDICATIONS AND USAGE section.

Gram-positive Organisms:

Corynebacterium diphtheriae
Corynebacterium minutissimum
Listeria monocytogenes
Staphylococcus aureus (resistant organisms may emerge during treatment)
Streptococcus pneumoniae
Streptococcus pyogenes

Gram-negative Organisms:

Bordetella pertussis
Legionella pneumophila
Neisseria gonorrhoeae

Other Microorganisms:

Chlamydia trachomatis
Entamoeba histolytica
Mycoplasma pneumoniae
Treponema pallidum
Ureaplasma urealyticum

The following in vitro data are available.

Erythromycin exhibits in vitro minimal inhibitory concentrations (MIC's) of 0.5 µg/mL or less against most (≥ 90%) strains of the following microorganisms; however, the safety and effectiveness of erythromycin in treating clinical infections due to these microorganisms have not been established in adequate and well-controlled clinical trials.

Gram-positive Organisms:

Viridans group streptococci

Gram-negative Organisms:

Moraxella catarrhalis

Susceptibility Testing

For specific information regarding susceptibility test interpretive criteria and associated test methods and quality control standards recognized by FDA for this drug, please see: https://www.fda.gov/STIC.

INDICATIONS AND USAGE

To reduce the development of drug-resistant bacteria and maintain the effectiveness of Ery-Ped and other antibacterial drugs, Ery-Ped should be used only to treat or prevent infections that are proven or strongly suspected to be caused by susceptible bacteria. When culture and susceptibility information are available, they should be considered in selecting or modifying antibacterial therapy. In the absence of such data, local epidemiology and susceptibility patterns may contribute to the empiric selection of therapy.

Ery-Ped is indicated in the treatment of infections caused by susceptible strains of the designated organisms in the diseases listed below:

Upper respiratory tract infections of mild to moderate degree caused by Streptococcus pyogenes, Streptococcus pneumoniae, or Haemophilus influenzae (when used concomitantly with adequate doses of sulfonamides, since many strains of H. influenzae are not susceptible to the erythromycin concentrations ordinarily achieved). (See appropriate sulfonamide labeling for prescribing information.)

Lower-respiratory tract infections of mild to moderate severity caused by Streptococcus pneumoniae or Streptococcus pyogenes.

Listeriosis caused by Listeria monocytogenes.

Pertussis (whooping cough) caused by Bordetella pertussis. Erythromycin is effective in eliminating the organism from the nasopharynx of infected
individuals rendering them noninfectious. Some clinical studies suggest that erythromycin may be helpful in the prophylaxis of pertussis in exposed
susceptible individuals.

Respiratory tract infections due to Mycoplasma pneumoniae.

Skin and skin structure infections of mild to moderate severity caused by Streptococcus pyogenes or Staphylococcus aureus (resistant staphylococci may emerge during treatment).

Diphtheria: Infections due to Corynebacterium diphtheriae, as an adjunct to antitoxin, to prevent establishment of carriers and to eradicate the organism in carriers.

Erythrasma: In the treatment of infections due to Corynebacterium minutissimum. Intestinal amebiasis caused by Entamoeba histolytica (oral erythromycins only). Extraenteric amebiasis requires treatment with other agents.

Acute Pelvic Inflammatory Disease caused by Neisseria gonorrhoeae: As an alternative drug in treatment of acute pelvic inflammatory disease caused by N. gonorrhoeae in female patients with a history of sensitivity to penicillin. Patients should have a serologic test for syphilis before receiving erythromycin as treatment of gonorrhea and a follow-up serologic test for syphilis after 3 months.

Syphilis caused by Treponema pallidum: Erythromycin is an alternate choice of treatment for primary syphilis in penicillin-allergic patients. In primary syphilis, spinal fluid examinations should be done before treatment and as part of follow-up after therapy.

Erythromycins are indicated for the treatment of the following infections caused by Chlamydia trachomatis: Conjunctivitis of the newborn, pneumonia of infancy, and urogenital infections during pregnancy. When tetracyclines are contraindicated or not tolerated, erythromycin is indicated for the treatment of uncomplicated urethral, endocervical, or rectal infections in adults due to Chlamydia trachomatis.

When tetracyclines are contraindicated or not tolerated, erythromycin is indicated for the treatment of nongonococcal urethritis caused by Ureaplasma urealyticum.

Legionnaires’ Disease caused by Legionella pneumophila: Although no controlled clinical efficacy studies have been conducted, in vitro and limited
preliminary clinical data suggest that erythromycin may be effective in treating Legionnaires’ Disease.

Prophylaxis:

Prevention of Initial Attacks of Rheumatic Fever: Penicillin is considered by the American Heart Association to be the drug of choice in the prevention of initial attacks of rheumatic fever (treatment of Streptococcus pyogenes infections of the upper respiratory tract, e.g., tonsillitis or pharyngitis). Erythromycin is indicated for the treatment of penicillin-allergic patients.^1 The therapeutic dose should be administered for 10 days.

Prevention of Recurrent Attacks of Rheumatic Fever: Penicillin or sulfonamides are considered by the American Heart Association to be the drugs of choice in the prevention of recurrent attacks of rheumatic fever. In patients who are allergic to penicillin and sulfonamides, oral erythromycin is recommended by the American Heart Association in the long-term prophylaxis of Streptococcal pharyngitis (for the prevention of recurrent attacks of rheumatic fever).^1

CONTRAINDICATIONS

Erythromycin is contraindicated in patients with known hypersensitivity to this antibiotic.

Erythromycin is contraindicated in patients taking terfenadine, astemizole, pimozide, or cisapride (see PRECAUTIONS - Drug Interactions).

Do not use erythromycin concomitantly with HMG CoA reductase inhibitors (statins) that are extensively metabolized by CYP 3A4 (lovastatin or simvastatin), due to the increased risk of myopathy, including rhabdomyolysis.

WARNINGS

Hepatotoxicity:

There have been reports of hepatic dysfunction, including increased liver enzymes, and hepatocellular and/or cholestatic hepatitis, with or without jaundice, occurring in patients receiving oral erythromycin products.

QT Prolongation:

Erythromycin has been associated with prolongation of the QT interval and infrequent cases of arrhythmia. Cases of torsades de pointes have been spontaneously reported during postmarketing surveillance in patients receiving erythromycin. Fatalities have been reported. Erythromycin should be avoided in patients with known prolongation of the QT interval, patients with ongoing proarrhythmic conditions such as uncorrected hypokalemia or hypomagnesemia, clinically significant bradycardia, and in patients receiving Class IA (quinidine, procainamide) or Class III (dofetilide, amiodarone, sotalol) antiarrhythmic agents. Elderly patients may be more susceptible to drug-associated effects on the QT interval.

Syphilis in Pregnancy:

There have been reports suggesting that erythromycin does not reach the fetus in adequate concentration to prevent congenital syphilis. Infants born to women treated during pregnancy with oral erythromycin for early syphilis should be treated with an appropriate penicillin regimen.

Clostridium difficile associated diarrhea (CDAD) has been reported with use of nearly all antibacterial agents, including Ery-Ped, and may range in severity from mild diarrhea to fatal colitis. Treatment with antibacterial agents alters the normal flora of the colon leading to overgrowth of C. difficile.

C. difficile produces toxins A and B which contribute to the development of CDAD. Hypertoxin producing strains of C. difficile cause increased morbidity and mortality, as these infections can be refractory to antimicrobial therapy and may require colectomy. CDAD must be considered in all patients who present with diarrhea following antibiotic use. Careful medical history is necessary since CDAD has been reported to occur over two months after the administration of antibacterial agents.

If CDAD is suspected or confirmed, ongoing antibiotic use not directed against C. difficile may need to be discontinued. Appropriate fluid and electrolyte management, protein supplementation, antibiotic treatment of C. difficile, and surgical evaluation should be instituted as clinically indicated.

Drug Interactions

Serious adverse reactions have been reported in patients taking erythromycin concomitantly with CYP3A4 substrates. These include colchicine toxicity with colchicine; rhabdomyolysis with simvastatin, lovastatin, and atorvastatin; and hypotension with calcium channel blockers metabolized by CYP3A4 (e.g., verapamil, amlodipine, diltiazem) (see PRECAUTIONS – Drug Interactions).

There have been post-marketing reports of colchicine toxicity with concomitant use of erythromycin and colchicine. This interaction is potentially life-threatening, and may occur while using both drugs at their recommended doses (see PRECAUTIONS – Drug Interactions).

Rhabdomyolysis with or without renal impairment has been reported in seriously ill patients receiving erythromycin concomitantly with lovastatin. Therefore, patients receiving concomitant lovastatin and erythromycin should be carefully monitored for creatine kinase (CK) and serum transaminase levels. (See package insert for lovastatin.)

PRECAUTIONS

GENERAL PRECAUTIONS

General: Prescribing Ery-Ped in the absence of a proven or strongly suspected bacterial infection or a prophylactic indication is unlikely to provide benefit to the patient and increases the risk of the development of drug-resistant bacteria.

Since erythromycin is principally excreted by the liver, caution should be exercised when erythromycin is administered to patients with impaired hepatic function (see CLINICAL PHARMACOLOGY and WARNINGS sections).

Exacerbation of symptoms of myasthenia gravis and new onset of symptoms of myasthenic syndrome has been reported in patients receiving erythromycin therapy.

There have been reports of infantile hypertrophic pyloric stenosis (IHPS) occurring in infants following erythromycin therapy. In one cohort of 157 newborns who were given erythromycin for pertussis prophylaxis, seven neonates (5%) developed symptoms of non-bilious vomiting or irritability with feeding and were subsequently diagnosed as having IHPS requiring surgical pyloromyotomy. A possible dose-response effect was described with an absolute risk of IHPS of 5.1% for infants who took erythromycin for 8-14 days and 10% for infants who took erythromycin for 15-21 days.^2 Since erythromycin may be used in the treatment of conditions in infants which are associated with significant mortality or morbidity (such as pertussis or neonatal Chlamydia trachomatis infections), the benefit of erythromycin therapy needs to be weighed against the potential risk of developing IHPS. Parents should be informed to contact their physician if vomiting or irritability with feeding occurs.

Prolonged or repeated use of erythromycin may result in an overgrowth of nonsusceptible bacteria or fungi. If superinfection occurs, erythromycin should be discontinued and appropriate therapy instituted.

When indicated, incision and drainage or other surgical procedures should be performed in conjunction with antibiotic therapy. Observational studies in humans have reported cardiovascular malformations after exposure to drug products containing erythromycin during early pregnancy.

PATIENT COUNSELING INFORMATION

Information for Patients: Patients should be counseled that antibacterial drugs, including Ery-Ped, should only be used to treat bacterial infections. They do not treat viral infections (e.g., the common cold). When Ery-Ped is prescribed to treat a bacterial infection, patients should be told that although it is common to feel better early in the course of therapy, the medication should be taken exactly as directed. Skipping doses or not completing the full course of therapy may (1) decrease the effectiveness of the immediate treatment and (2) increase the likelihood that bacteria will develop resistance and will not be treatable by Ery-Ped or other antibacterial drugs in the future.

Diarrhea is a common problem caused by antibiotics which usually ends when the antibiotic is discontinued. Sometimes after starting treatment with antibiotics, patients can develop watery and bloody stools (with or without stomach cramps and fever) even as late as two or more months after having taken the last dose of the antibiotic. If this occurs, patients should contact their physician as soon as possible.

Drug Interactions

Theophylline:

Erythromycin use in patients who are receiving high doses of theophylline may be associated with an increase in serum theophylline levels and potential theophylline toxicity. In case of theophylline toxicity and/or elevated serum theophylline levels, the dose of theophylline should be reduced while the patient is receiving concomitant erythromycin therapy.

There have been published reports suggesting that when oral erythromycin is given concurrently with theophylline there is a decrease in erythromycin serum concentrations of approximately 35%. The mechanism by which this interaction occurs is unknown. The decrease in erythromycin concentrations due to co-administration of theophylline could result in subtherapeutic concentrations of erythromycin.

Hypotension, bradyarrhythmias, and lactic acidosis have been observed in patients receiving concurrent verapamil, belonging to the calcium channel blockers drug class.

Concomitant administration of erythromycin and digoxin has been reported to result in elevated digoxin serum levels.

There have been reports of increased anticoagulant effects when erythromycin and oral anticoagulants were used concomitantly. Increased anticoagulation effects due to interactions of erythromycin with various oral anticoagulants may be more pronounced in the elderly.

Erythromycin is a substrate and inhibitor of the 3A isoform subfamily of the cytochrome p450 enzyme system (CYP3A). Coadministration of erythromycin and a drug primarily metabolized by CYP3A may be associated with elevations in drug concentrations that could increase or prolong both the therapeutic and adverse effects of the concomitant drug. Dosage adjustments may be considered, and when possible, serum concentrations of drugs primarily metabolized by CYP3A should be monitored closely in patients concurrently receiving erythromycin.

The following are examples of some clinically significant CYP3A based drug interactions. Interactions with other drugs metabolized by the CYP3A isoform are also possible. The following CYP3A based drug interactions have been observed with erythromycin products in post-marketing experience:

Ergotamine/dihydroergotamine: Post-marketing reports indicate that coadministration of erythromycin with ergotamine or dihydroergotamine has been associated with acute ergot toxicity characterized by vasospasm and ischemia of the extremities and other tissues including the central nervous system. Concomitant administration of erythromycin with ergotamine or dihydroergotamine is contraindicated (see CONTRAINDICATIONS).

Triazolobenzodiazepines: (such as triazolam and alprazolam) and Related Benzodiazepines: Erythromycin has been reported to decrease the clearance of triazolam and midazolam, and thus, may increase the pharmacologic effect of these benzodiazepines.

HMG-CoA Reductase Inhibitors: Erythromycin has been reported to increase concentrations of HMG-CoA reductase inhibitors (e.g., lovastatin and simvastatin). Rare reports of rhabdomyolysis have been reported in patients taking these drugs concomitantly.

Sildenafil (Viagra): Erythromycin has been reported to increase the systemic exposure (AUC) of sildenafil. Reduction of sildenafil dosage should be considered. (See Viagra package insert.)

There have been spontaneous or published reports of CYP3A based interactions of erythromycin with cyclosporine, carbamazepine, tacrolimus, alfentanil, disopyramide, rifabutin, quinidine, methylprednisolone, cilostazol, vinblastine, and bromocriptine.

Concomitant administration of erythromycin with cisapride, pimozide, astemizole, or terfenadine is contraindicated (see CONTRAINDICATIONS.)

In addition, there have been reports of interactions of erythromycin with drugs not thought to be metabolized by CYP3A, including hexobarbital, phenytoin, and valproate.

Erythromycin has been reported to significantly alter the metabolism of the nonsedating antihistamines terfenadine and astemizole when taken concomitantly. Rare cases of serious cardiovascular adverse events, including electrocardiographic QT/QTc interval prolongation, cardiac arrest, torsades de pointes, and other ventricular arrhythmias have been observed (see CONTRAINDICATIONS). In addition, deaths have been reported rarely with concomitant administration of terfenadine and erythromycin.

There have been post-marketing reports of drug interactions when erythromycin was co-administered with cisapride, resulting in QT prolongation, cardiac arrhythmias, ventricular tachycardia, ventricular fibrillation, and torsades de pointes most likely due to the inhibition of hepatic metabolism of cisapride by erythromycin. Fatalities have been reported (see CONTRAINDICATIONS).

Colchicine: Colchicine is a substrate for both CYP3A4 and the efflux transporter P-glycoprotein (P-gp). Erythromycin is considered a moderate inhibitor of CYP3A4. A significant increase in colchicine plasma concentration is anticipated when co-administered with moderate CYP3A4 inhibitors such as erythromycin. If co-administration of colchicine and erythromycin is necessary, the starting dose of colchicine may need to be reduced, and the maximum colchicine dose should be lowered. Patients should be monitored for clinical symptoms of colchicine toxicity (see WARNINGS).

DRUG AND OR LABORATORY TEST INTERACTIONS

Drug/Laboratory Test Interactions: Erythromycin interferes with the fluorometric determination of urinary catecholamines.

CARCINOGENESIS AND MUTAGENESIS AND IMPAIRMENT OF FERTILITY

Carcinogenesis, Mutagenesis, Impairment of Fertility: Long-term oral dietary studies conducted with erythromycin stearate in rats up to 400 mg/kg/day and in mice up to 500 mg/kg/day (approximately 1-2 fold of the maximum human dose on a body surface area basis) did not provide evidence of tumorigenicity. Erythromycin stearate did not show genotoxic potential in the Ames, and mouse lymphoma assays or induce chromosomal aberrations in CHO cells. There was no apparent effect on male or female fertility in rats treated with erythromycin base by oral gavage at 700 mg/kg/day (approximately 3 times the maximum human dose on a body surface area basis).

PREGNANCY

TERATOGENIC EFFECTS

Pregnancy: Teratogenic Effects. There is no evidence of teratogenicity or any other adverse effect on reproduction in female rats fed erythromycin base by oral gavage at 350 mg/kg/day (approximately twice the maximum recommended human dose on a body surface area) prior to and during mating, during gestation, and through weaning. No evidence of teratogenicity or embryotoxicity was observed when erythromycin base was given by oral gavage to pregnant rats and mice at 700 mg/kg/day and to pregnant rabbits at 125 mg/kg/day (approximately 1-3 times the maximum recommended human dose).

Labor and Delivery: The effect of erythromycin on labor and delivery is unknown.

NURSING MOTHERS

Nursing Mothers: Erythromycin is excreted in human milk. Caution should be exercised when erythromycin is administered to a nursing woman.

PEDIATRIC USE

Pediatric Use: See INDICATIONS AND USAGE and DOSAGE AND ADMINISTRATION sections.

GERIATRIC USE

Geriatric Use: Elderly patients, particularly those with reduced renal or hepatic function, may be at increased risk for developing erythromycin-induced hearing loss (see ADVERSE REACTIONS and DOSAGE AND ADMINISTRATION).

Elderly patients may be more susceptible to development of torsades de pointes arrhythmias than younger patients (see WARNINGS).

Elderly patients may experience increased effects of oral anticoagulant therapy while undergoing treatment with erythromycin (see PRECAUTIONS - Drug Interactions).

Ery-Ped 200 contains 117.5 mg (5.1 mEq) of sodium per individual dose.

Ery-Ped 400 contains 117.5 mg (5.1 mEq) of sodium per individual dose.

Based on the 200 mg/5 mL strength, at the usual recommended doses, adult patients would receive a total of 940 mg/day (40.8 mEq) of sodium. Based on the 400 mg/5 mL strength, at the usual recommended doses, adult patients would receive a total of 470 mg/day (20.4 mEq) of sodium. The geriatric population may respond with a blunted natriuresis to salt loading. This may be clinically important with regard to such diseases as congestive heart failure.

ADVERSE REACTIONS

The most frequent side effects of oral erythromycin preparations are gastrointestinal and are dose-related. They include nausea, vomiting, abdominal pain, diarrhea and anorexia. Symptoms of hepatitis, hepatic dysfunction and/or abnormal liver function test results may occur (see WARNINGS section).

Onset of pseudomembranous colitis symptoms may occur during or after antibacterial treatment (see WARNINGS).

Erythromycin has been associated with QT prolongation and ventricular arrhythmias, including ventricular tachycardia and torsades de pointes (see WARNINGS).

Allergic reactions ranging from urticaria to anaphylaxis have occurred. Skin reactions ranging from mild eruptions to erythema multiforme, Stevens-Johnson syndrome, and toxic epidermal necrolysis have been reported rarely.

There have been reports of interstitial nephritis coincident with erythromycin use.

There have been rare reports of pancreatitis and convulsions.

There have been isolated reports of reversible hearing loss occurring chiefly in patients with renal insufficiency and in patients receiving high doses of erythromycin.

OVERDOSAGE

In case of overdosage, erythromycin should be discontinued. Overdosage should be handled with the prompt elimination of unabsorbed drug and all other appropriate measures should be instituted.

Erythromycin is not removed by peritoneal dialysis or hemodialysis.

DOSAGE AND ADMINISTRATION

Ery-Ped (erythromycin ethylsuccinate) oral suspensions may be administered without regard to meals.

Children: Age, weight, and severity of the infection are important factors in determining the proper dosage. In mild to moderate infections, the usual dosage of erythromycin ethylsuccinate for children is 30 to 50 mg/kg/day in equally divided doses every 6 hours. For more severe infections this dosage may be doubled. If twice-a-day dosage is desired, one-half of the total daily dose may be given every 12 hours. Doses may also be given three times daily by administering one-third of the total daily dose every 8 hours.

The following dosage schedule is suggested for mild to moderate infections:

Body Weight | Total Daily Dose
Under 10 lbs | 30-50 mg/kg/day 15-25 mg/lb/day
10 to 15 lbs | 200 mg
16 to 25 lbs | 400 mg
26 to 50 lbs | 800 mg
51 to 100 lbs | 1200 mg
over 100 lbs | 1600 mg

Adults: 400 mg erythromycin ethylsuccinate every 6 hours is the usual dose. Dosage may be increased up to 4 g per day according to the severity of the infection. If twice-a-day dosage is desired, one-half of the total daily dose may be given every 12 hours. Doses may also be given three times daily by administering one-third of the total daily dose every 8 hours.

For adult dosage calculation, use a ratio of 400 mg of erythromycin activity as the ethylsuccinate to 250 mg of erythromycin activity as the stearate, base or estolate.

In the treatment of streptococcal infections, a therapeutic dosage of erythromycin ethylsuccinate should be administered for at least 10 days. In continuous prophylaxis against recurrences of streptococcal infections in persons with a history of rheumatic heart disease, the usual dosage is 400 mg twice a day.

For treatment of urethritis due to C. trachomatis or U. urealyticum: 800 mg three times a day for 7 days.

For treatment of primary syphilis: Adults: 48 to 64 g given in divided doses over a period of 10 to 15 days.

For intestinal amebiasis: Adults: 400 mg four times daily for 10 to 14 days.

Children: 30 to 50 mg/kg/day in divided doses for 10 to 14 days.

For use in pertussis: Although optimal dosage and duration have not been established, doses of erythromycin utilized in reported clinical studies were 40 to 50 mg/kg/day, given in divided doses for 5 to 14 days.

For treatment of Legionnaires' Disease: Although optimal doses have not been established, doses utilized in reported clinical data were 1.6 to 4 g daily in divided doses.

HOW SUPPLIED

Ery-Ped 200 (erythromycin ethylsuccinate for oral suspension, USP) is supplied in bottles of 100 mL (NDC 80005-154-18).

Ery-Ped 400 (erythromycin ethylsuccinate for oral suspension, USP) is supplied in bottles of 100 mL (NDC 80005-155-18).

Recommended Storage:

Store Ery-Ped 200 and Ery-Ped 400, prior to mixing, below 86°F (30°C). After reconstitution, Ery-Ped 200 and Ery-Ped 400 must be stored at or below 77°F (25°C) and used within 35 days; refrigeration is not required.

REFERENCES

1. Committee on Rheumatic Fever, Endocarditis, and Kawasaki Disease of the Council on Cardiovascular Disease in the Young, the American Heart Association: Prevention of Rheumatic Fever. Circulation. 78(4):1082-1086, October 1988.
2. Honein, M.A., et al.: Infantile hypertrophic pyloric stenosis after pertussis prophylaxis with erythromycin: a case review and cohort study. The Lancet 1999;354 (9196): 2101-5

Rev. 12/2024

Carnegie Pharmaceuticals LLC
Delran, NJ 08075, USA

PRINCIPAL DISPLAY PANEL - 400 mg per 5 mL Bottle Label

NDC 80005-155-18
100 mL For Oral Suspension
(when mixed)

EryPed® 400

ERYTHROMYCIN
ETHYLSUCCINATE FOR
ORAL SUSPENSION, USP

Erythromycin activity

400 mg per 5 mL
when reconstituted

Rx only

Carnegie Pharma